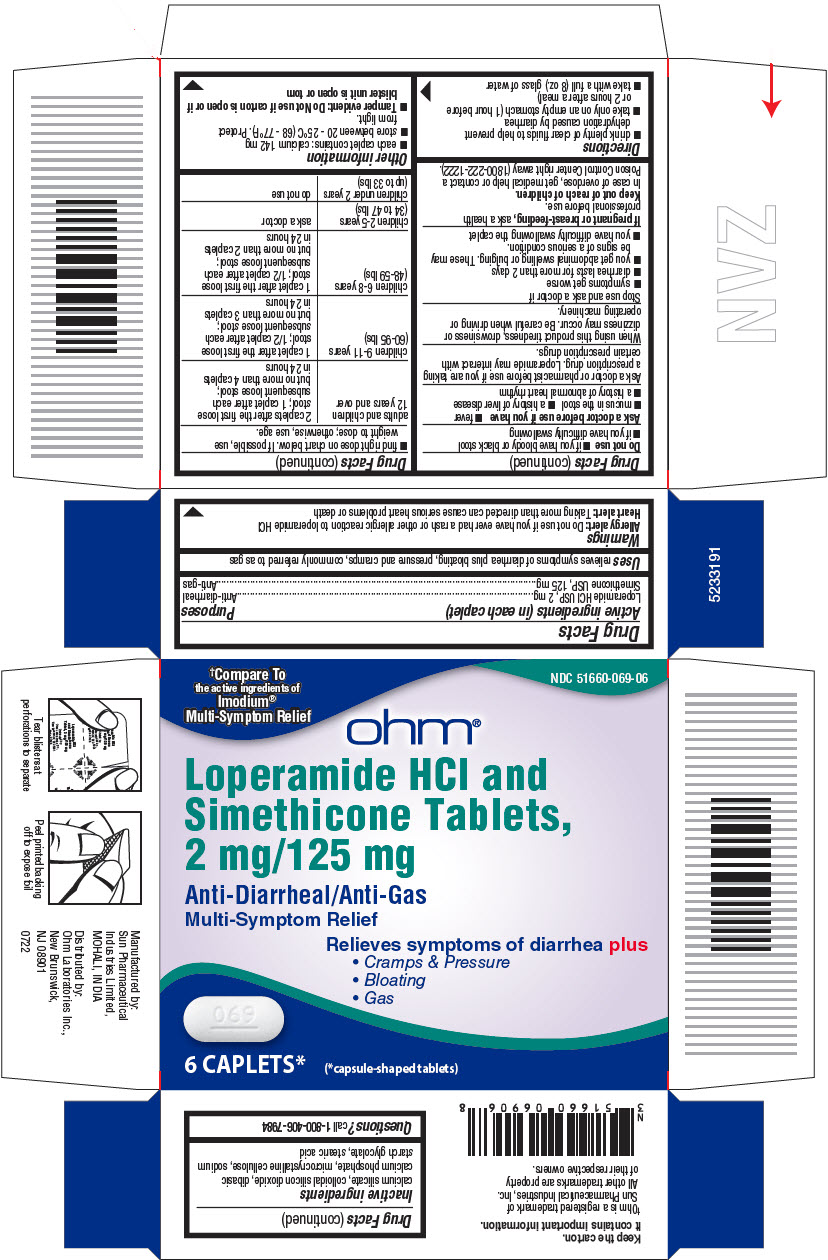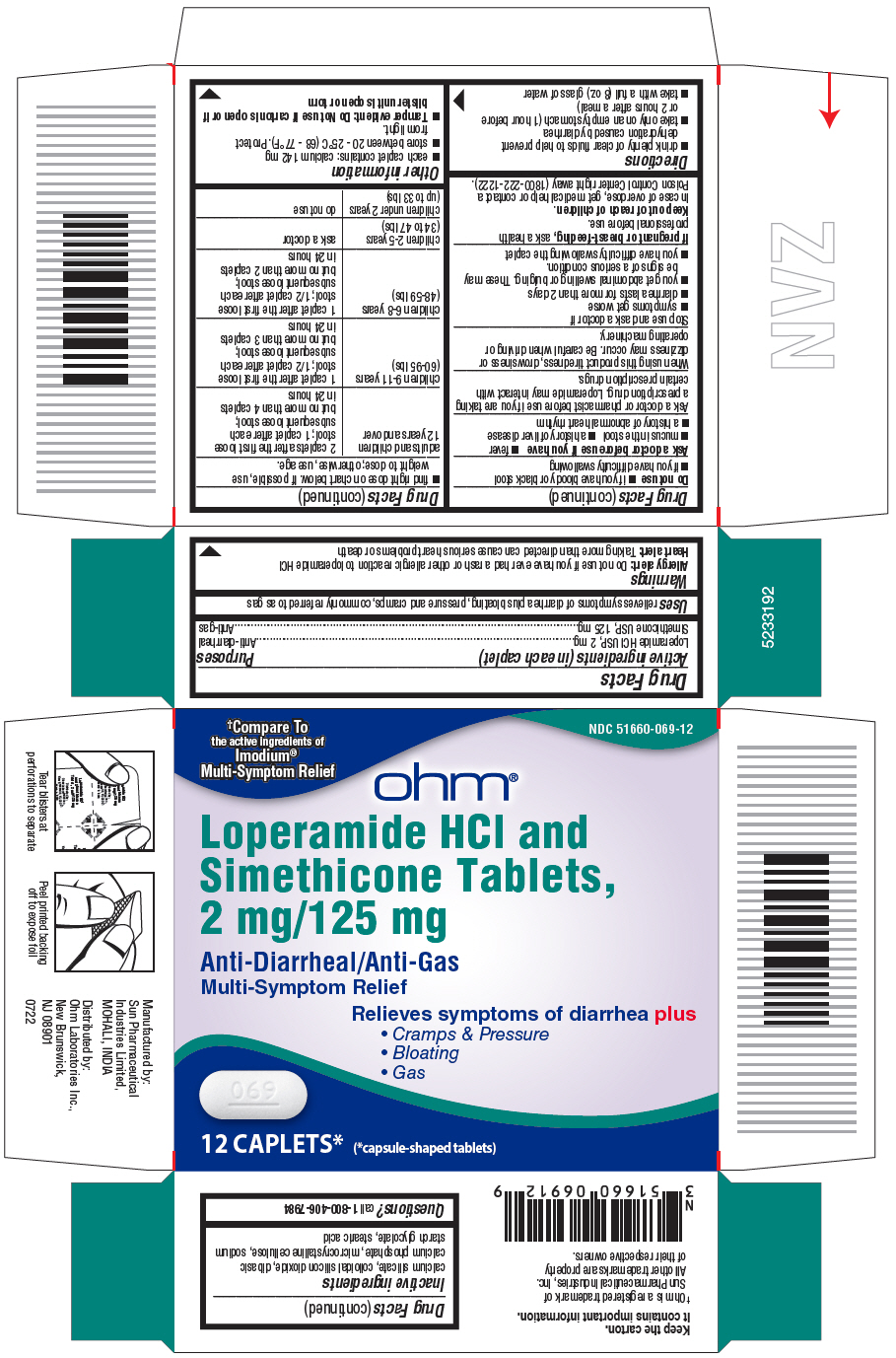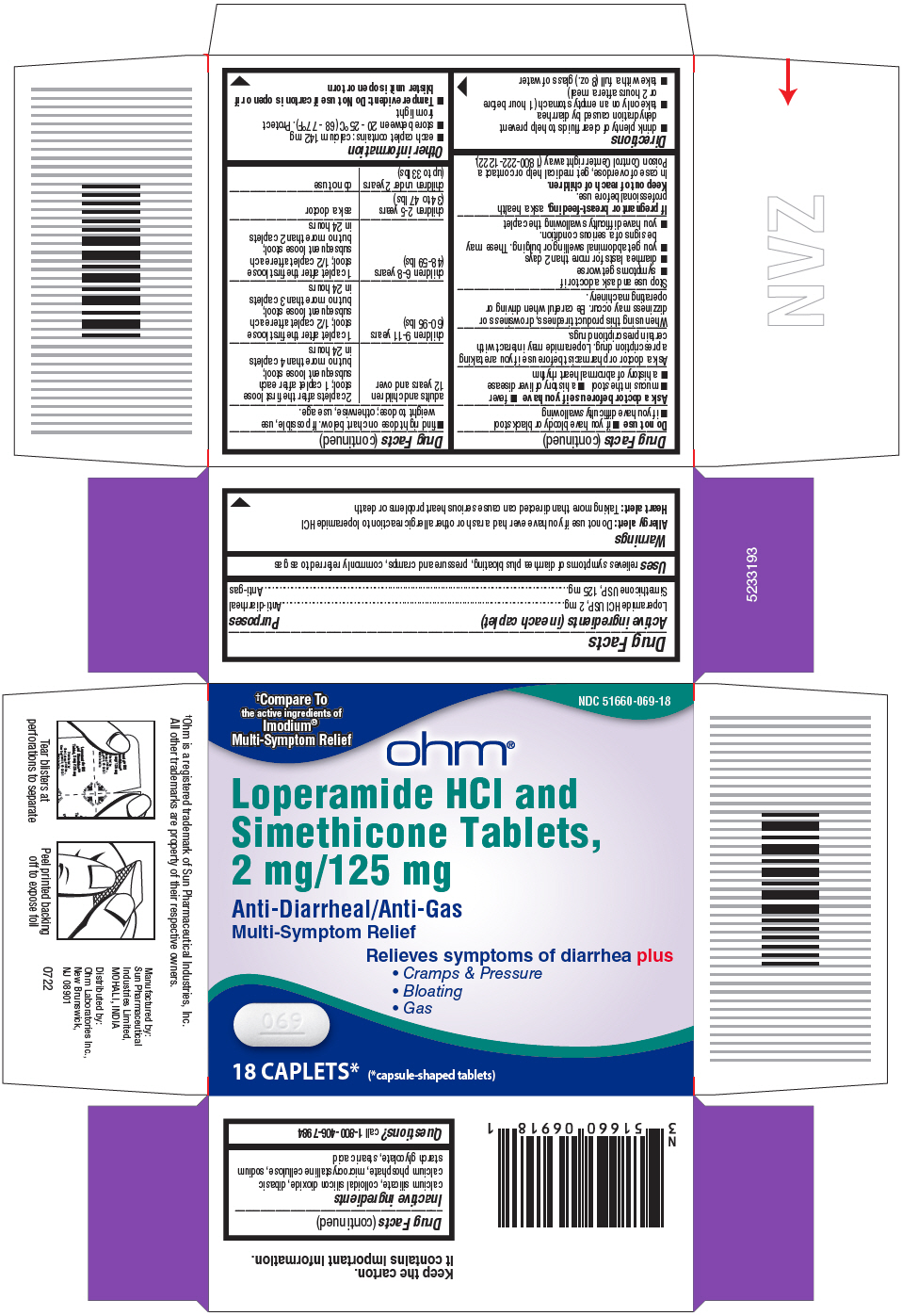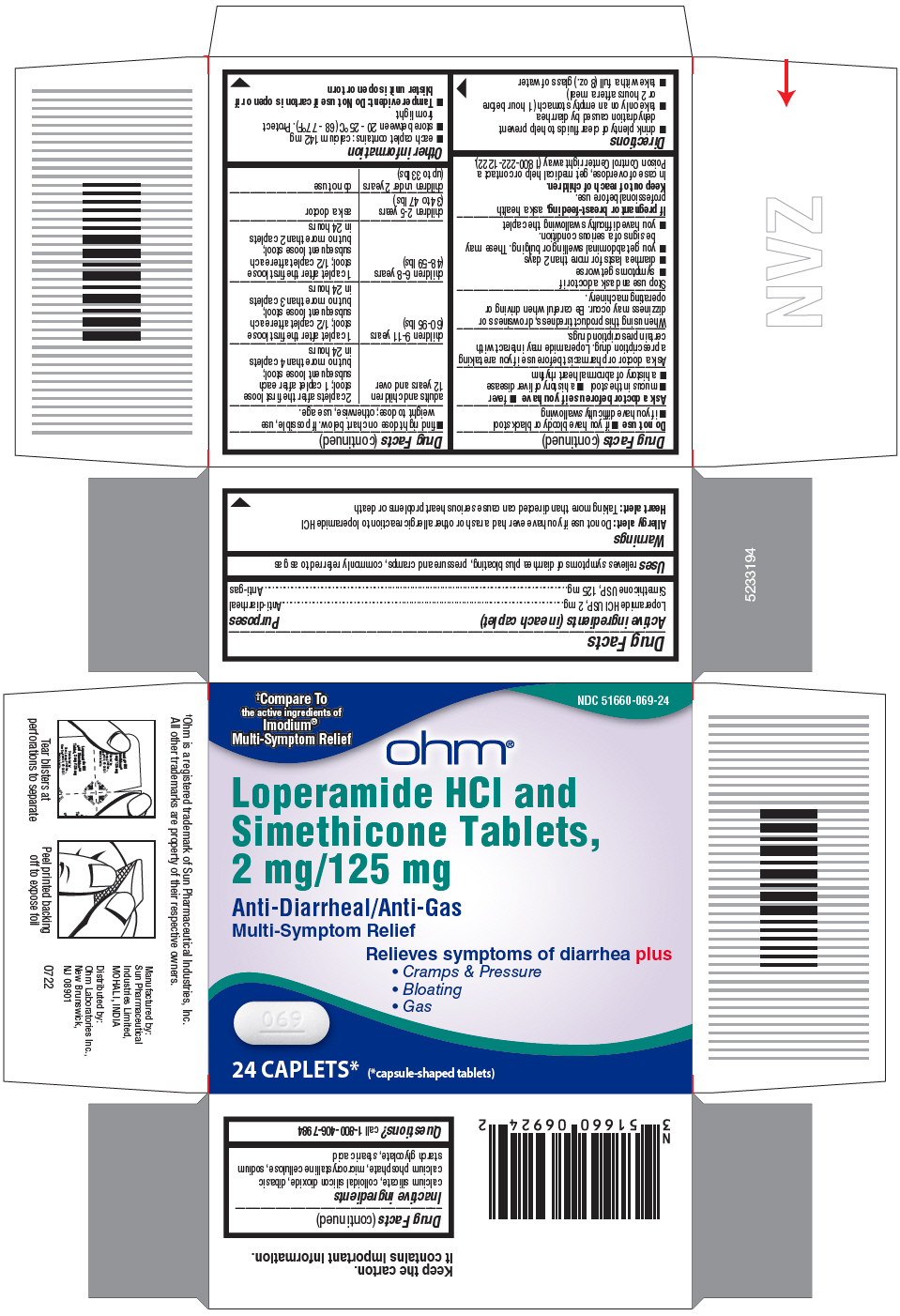 DRUG LABEL: Loperamide HCl and Simethicone
NDC: 51660-069 | Form: TABLET
Manufacturer: Ohm Laboratories Inc.
Category: otc | Type: HUMAN OTC DRUG LABEL
Date: 20220830

ACTIVE INGREDIENTS: LOPERAMIDE HYDROCHLORIDE 2 mg/1 1; DIMETHICONE 125 mg/1 1
INACTIVE INGREDIENTS: CALCIUM SILICATE; SILICON DIOXIDE; ANHYDROUS DIBASIC CALCIUM PHOSPHATE; MICROCRYSTALLINE CELLULOSE; STEARIC ACID; SODIUM STARCH GLYCOLATE TYPE A POTATO

Drug Facts

Active ingredients (in each caplet)

Loperamide HCl USP, 2 mg

Simethicone USP, 125 mg

Purposes

Anti-diarrheal

Anti-gas

Uses

relieves symptoms of diarrhea plus bloating, pressure and cramps, commonly referred to as gas

Warnings

Allergy alert:

Do not use if you have ever had a rash or other allergic reaction to loperamide HCl

Heart Alert: Taking more than directed can cause serious heart problems or death

Do not use

- if you have bloody or black stool
- if you have difficulty swallowing

Ask a doctor before use if you have

- fever
- mucus in the stool
- a history of liver disease
- a history of abnormal heart rhythm

Ask a doctor or pharmacist before use if you are

taking a prescription drug. Loperamide may interact with certain prescription drugs.

When using this product

tiredness, drowsiness or dizziness may occur. Be careful when driving or operating machinery.

Stop use and ask a doctor if

- symptoms get worse
- diarrhea lasts for more than 2 days
- you get abdominal swelling or bulging. These may be signs of a serious condition.
- you have difficulty swallowing the caplet

If pregnant or breast-feeding,

ask a health professional before use.

Keep out of reach of children.

In case of overdose, get medical help or contact a Poison Control Center right away (1800-222-1222).

Directions

- drink plenty of clear fluids to help prevent dehydration caused by diarrhea
- take only on an empty stomach (1 hour before or 2 hours after a meal)
- take with a full (8 oz.) glass of water
- find right dose on chart below. If possible, use weight to dose; otherwise, use age.

adults and children 12 years and over | 2 caplets after the first loose; stool; 1 caplet after each; subsequent loose stool;; but no more than 4 caplets in 24 hours
children 9-11 years (60-95 lbs) | 1 caplet after the first loose; stool; 1/2 caplet after each; subsequent loose stool;; but no more than 3 caplets in 24 hours
children 6-8 years (48-59 lbs) | 1 caplet after the first loose; stool; 1/2 caplet after each; subsequent loose stool;; but no more than 2 caplets in 24 hours
children 2-5 years (34 to 47 lbs) | ask a doctor
children under 2 years (upto 33 lbs) | do not use

Other information

- calcium: contains 142 mg/caplet
- store between 20-25° C (68-77° F). Protect from light.
- TAMPER EVIDENT: THIS PRODUCT PROTECTED WITH SEALED BLISTER UNITS. DO NOT USE IF ANY ARE TORN OR BROKEN.

Inactive ingredients

calcium silicate, colloidal silicon dioxide, dibasic calcium phosphate, microcrystalline cellulose, sodium starch glycolate, stearic acid

Questions?

call 1-800-406-7984

Manufactured by:
Sun Pharmaceutical
Industries Limited,
MOHALI, INDIA

Distributed by:
Ohm Laboratories Inc.,
New Brunswick,
NJ 08901

PRINCIPAL DISPLAY PANEL - 6 Capsule Blister Pack Carton

†Compare To
the active ingredients of
Imodium®
Multi-Symptom Relief

NDC 51660-069-06

ohm®

Loperamide HCl and
Simethicone Tablets,
2 mg/125 mg

Anti-Diarrheal/Anti-Gas
Multi-Symptom Relief

Relieves symptoms of diarrhea plus

- Cramps & Pressure
- Bloating
- Gas

6 CAPLETS*
(*capsule-shaped tablets)

PRINCIPAL DISPLAY PANEL - 12 Caplet Blister Pack Carton

†Compare To
the active ingredients of
Imodium®
Multi-Symptom Relief

NDC 51660-069-12

ohm®

Loperamide HCl and
Simethicone Tablets,
2 mg/125 mg

Anti-Diarrheal/Anti-Gas
Multi-Symptom Relief

Relieves symptoms of diarrhea plus

- Cramps & Pressure
- Bloating
- Gas

12 CAPLETS*
(*capsule-shaped tablets)

PRINCIPAL DISPLAY PANEL - 18 Caplet Blister Pack Carton

†Compare To
the active ingredients of
Imodium®
Multi-Symptom Relief

NDC 51660-069-18

ohm®

Loperamide HCl and
Simethicone Tablets,
2 mg/125 mg

Anti-Diarrheal/Anti-Gas
Multi-Symptom Relief

Relieves symptoms of diarrhea plus

- Cramps & Pressure
- Bloating
- Gas

18 CAPLETS*
(*capsule-shaped tablets)

PRINCIPAL DISPLAY PANEL - 24 Caplet Blister Pack Carton

†Compare To
the active ingredients of
Imodium®
Multi-Symptom Relief

NDC 51660-069-24

ohm®

Loperamide HCl and
Simethicone Tablets,
2 mg/125 mg

Anti-Diarrheal/Anti-Gas
Multi-Symptom Relief

Relieves symptoms of diarrhea plus

- Cramps & Pressure
- Bloating
- Gas

24 CAPLETS*
(*capsule-shaped tablets)